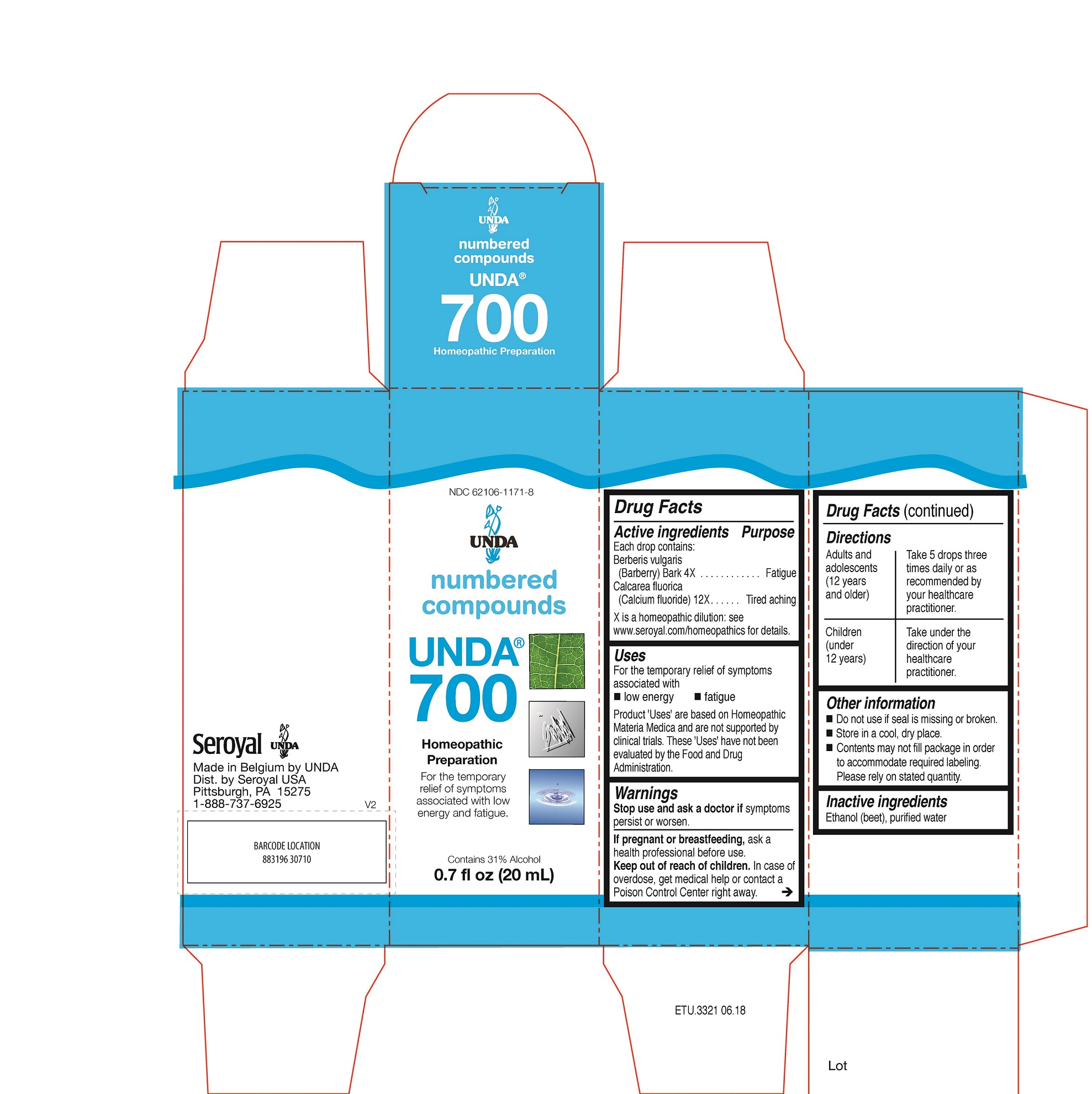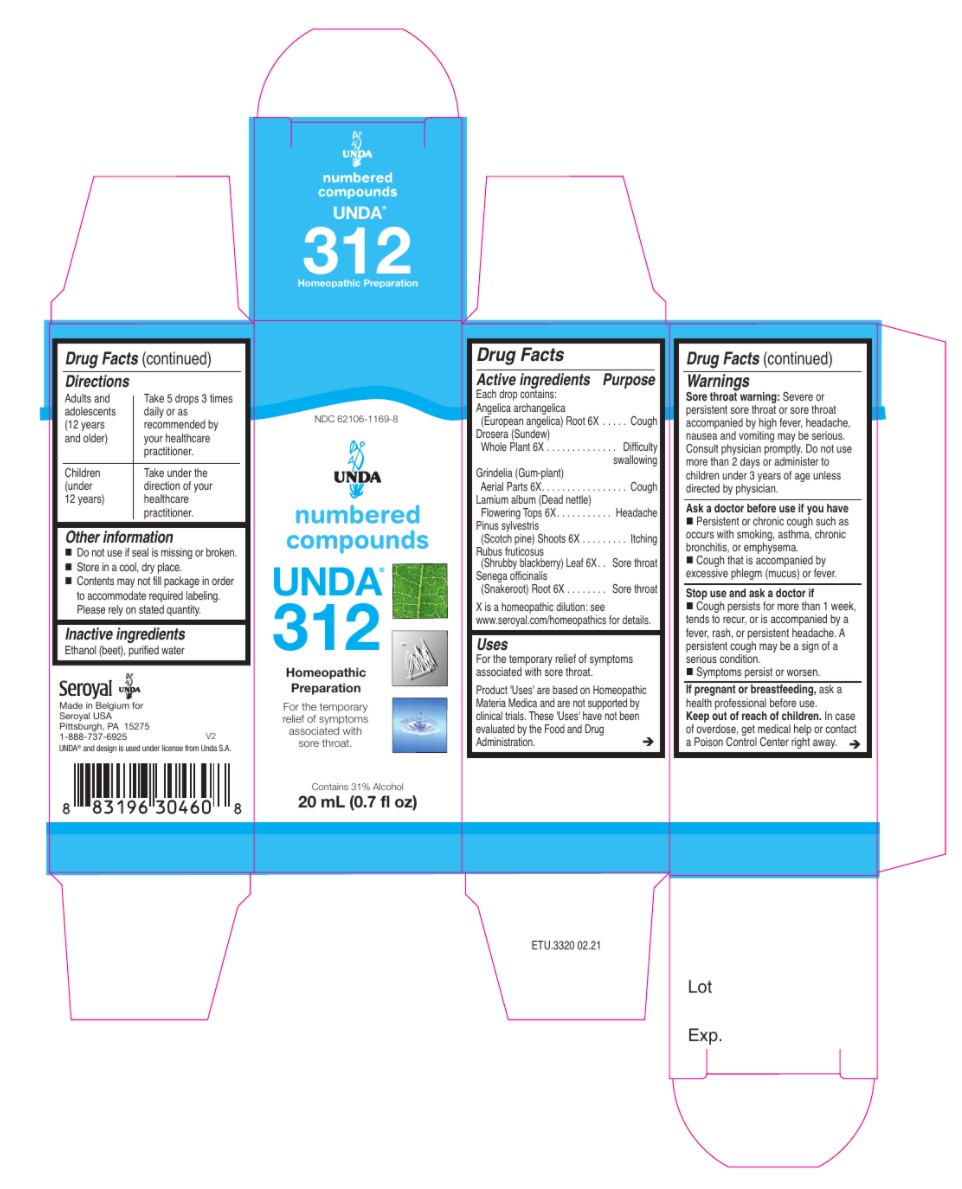 DRUG LABEL: UNDA 700
NDC: 62106-1171 | Form: LIQUID
Manufacturer: Seroyal USA
Category: homeopathic | Type: HUMAN OTC DRUG LABEL
Date: 20210715

ACTIVE INGREDIENTS: BERBERIS VULGARIS ROOT BARK 4 [hp_X]/20 mL; CALCIUM FLUORIDE 12 [hp_X]/20 mL
INACTIVE INGREDIENTS: ALCOHOL; WATER

UNDA 312 and 700

Active ingredients

Each drop contains:

Angelica archangelica (European angelica) Root 6X
Drosera (Sundew) Whole Plant 6X
Grindelia (Gum-plant) Aerial Parts 6X
Lamium album (Dead nettle) Aerial Parts 6X
Pinus sylvestris (Scotch pine) Shoots 6X
Rubus fruticosus (Shrubby blackberry) Leaf 6X
Senega officinalis (Snakeroot) Root 6X

Uses
For the relief of symptoms associated with sore throat.

Warnings
Sore throat warning: Severe or persistent sore throat or sore throat accompanied by high fever, headache,
nausea and vomiting may be serious.
Consult physician promptly.

Do not use more than 2 days or administer to children under 3 years of age unless directed by physician.

Ask a doctor before use if you have Persistent or chronic cough such as occurs with smoking, asthma, chronic
bronchitis, or emphysema.
Cough that is accompanied by excessive phlegm (mucus) or fever.

Stop use and ask a doctor if Cough persists for more than 1 week, tends to recur, or is accompanied by a
fever, rash, or persistent headache. A persistent cough may be a sign of a serious condition.

Stop use and ask a doctor if symptoms persist or worsen.

If pregnant or breastfeeding, ask a health professional before use.
Keep out of reach of children.

In case of overdose, get medical help or contact a Poison Control Center right away.

Ask a doctor before use if you have Persistent or chronic cough such as occurs with smoking, asthma, chronic

bronchitis, or emphysema.
Cough that is accompanied by excessive phlegm (mucus) or fever.

Stop use and ask a doctor if Cough persists for more than 1 week, tends to recur, or is accompanied by a

fever, rash, or persistent headache. A persistent cough may be a sign of a serious condition.

Stop use and ask a doctor if symptoms persist or worsen.

Do not use more than 2 days or administer to children under 3 years of age unless directed by physician.

PREGNANCY OR BREAST FEEDING

If pregnant or breastfeeding, ask a health professional before use.

Keep out of reach of children.

OVERDOSAGE

In case of overdose, get medical help or contact a Poison Control Center right away.

Inactive ingredients
Ethanol (beet), purified water

Other information
Do not use if seal is missing or broken.
Store in a cool, dry place.

Contents may not fill package in order
to accommodate required labeling.
Please rely on stated quantity.

Directions
Adults and adolescents (12 years and older): Take 5 drops three times daily or as
recommended by your healthcare practitioner.
Children (under 12 years): Take under the direction of your
healthcare practitioner.

Uses
For the relief of symptoms associated with sore throat.

Directions
Adults and adolescents (12 years and older): Take 5 drops three times daily or as
recommended by your healthcare practitioner.
Children (under 12 years): Take under the direction of your
healthcare practitioner.

Active ingredients

Each drop contains equal parts of:

Berberis vulgaris (Barberry) Bark 4X
Calcarea fluorica (Calcium fluoride) 12X

Uses
For the relief of symptoms associated with low energy and fatigue

Warnings
Stop use and ask a doctor if symptoms persist or worsen.
If pregnant or breastfeeding, ask a health professional before use.
Keep out of reach of children.
In case of overdose, get medical help or contact a Poison Control Center right away.

Stop use and ask a doctor if symptoms persist or worsen.

PREGNANCY OR BREAST FEEDING

If pregnant or breastfeeding, ask a health professional before use.

Keep out of reach of children.

OVERDOSAGE

In case of overdose, get medical help or contact a Poison Control Center right away.

Inactive ingredients
Ethanol (beet), purified water

Other information
Do not use if seal is missing or broken.
Store in a cool, dry place.

Directions
Adults and adolescents (12 years and older): Take 5 drops three times daily or as
recommended by your healthcare practitioner.
Children (under 12 years): Take under the direction of your
healthcare practitioner.

Uses
For the relief of symptoms associated with low energy and fatigue

Directions
Adults and adolescents (12 years and older): Take 5 drops three times daily or as
recommended by your healthcare practitioner.
Children (under 12 years): Take under the direction of your
healthcare practitioner.

PACKAGE LABEL

UNDA
NDC 62106-1169-8
numbered compounds
UNDA 312
Homeopathic Preparation

For the relief of symptoms associated with sore throat.
Contains 31% Alcohol
0.7 fl oz (20 mL)

PACKAGE LABEL

UNDA
NDC 62106-1171-8
numbered compounds
UNDA 700
Homeopathic Preparation
Contains 31% Alcohol
0.7 fl oz (20 mL)